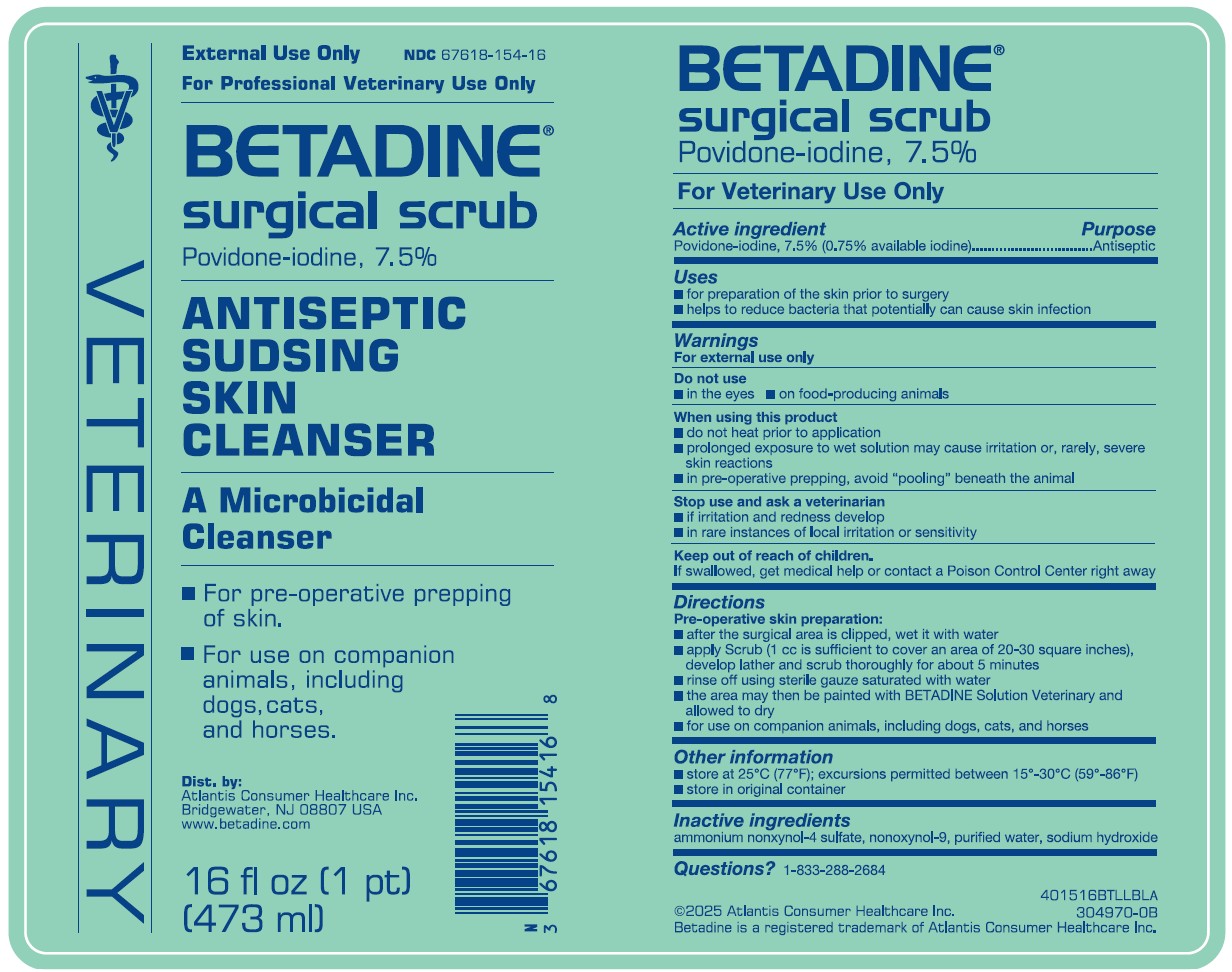 DRUG LABEL: Betadine Surgical Scrub
NDC: 67618-154 | Form: SOLUTION
Manufacturer: Atlantis Consumer Healthcare Inc
Category: animal | Type: OTC ANIMAL DRUG LABEL
Date: 20251229

ACTIVE INGREDIENTS: Povidone-Iodine 7.5 mg/1 mL
INACTIVE INGREDIENTS: Ammonium Nonoxynol-4 Sulfate; Nonoxynol-9; Water; Sodium Hydroxide

BETADINE®
surgical scrub
Povidone-iodine, 7. 5%
For Veterinary Use Only

Active ingredient

Povidone-iodine, 7.5% (0.75% available iodine)

Purpose

Antiseptic

Uses

- for preparation of the skin prior to surgery
- helps to reduce bacteria that potentially can cause skin infection

Warnings

For external use only

Do not use

- in the eyes
- on food-producing animals

When using this product

- do not heat prior to application
- prolonged exposure to wet solution may cause irritation or, rarely, severe skin reactions
- in pre-operative prepping, avoid "pooling" beneath the animal

Stop use and ask a veterinarian

- if irritation and redness develop
- in rare instances of local irritation or sensitivity

Keep out of reach of children.

If swallowed, get medical help or contact a Poison Control Center right away

Directions Pre-operative skin preparation:

- after the surgical area is clipped, wet it with water
- apply Scrub (1 cc is sufficient to cover an area of 20-30 square inches), develop lather and scrub thoroughly for about 5 minutes
- rinse off using sterile gauze saturated with water
- the area may then be painted with BETADINE Solution Veterinary and allowed to dry
- for use on companion animals, including dogs, cats, and horses

Other Information

- store at 25"C (77°F); excursions permitted between 15"-30"C (59°-86°F)
- store in original container

Inactive Ingredients

ammonium nonxynol-4 sulfate, nonoxynol-9, purified water, sodium hydroxide

Questions?

1-833-288-2684
©2025 Atlantis Consumer Healthcare Inc.
Betadine is a registered trademark of Atlantis Consumer Healthcare Inc.

Package Label

External Use Only NDC 67618-154-16
For Professional Veterinary Use Only
BETADINE®
surgical scrub
Povidone-iodine, 7.5%
ANTISEPTIC
SUDSING
SKIN
CLEANSER
A Microbicidal
Cleanser
■ For pre-operative prepping of skin.
■ For use on companion animals, including dogs, cats, and horses.
Dist. by:
Atlantis Consumer Healthcare Inc.
Bridgewater, NJ 08807 USA
www.betadine.com
16 fl oz (1 pt)
(473 ml)
401516BTLLBLA
304970-0B